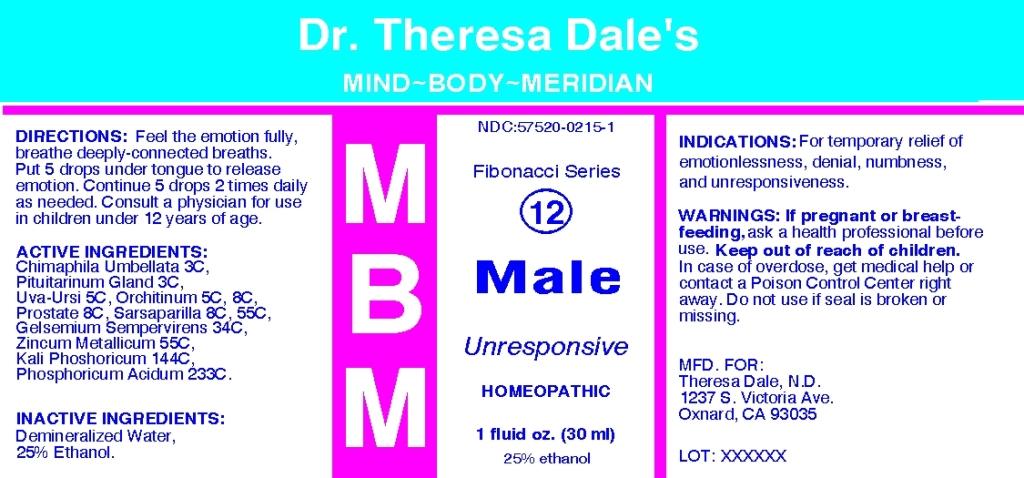 DRUG LABEL: MBM 12 Male Unresponsive
NDC: 57520-0215 | Form: LIQUID
Manufacturer: Apotheca Company
Category: homeopathic | Type: HUMAN OTC DRUG LABEL
Date: 20100816

ACTIVE INGREDIENTS: CHIMAPHILA UMBELLATA 3 [hp_C]/1 mL; SUS SCROFA PITUITARY GLAND 3 [hp_C]/1 mL; ARCTOSTAPHYLOS UVA-URSI LEAF 5 [hp_C]/1 mL; SUS SCROFA PROSTATE 8 [hp_C]/1 mL; SARSAPARILLA ROOT 55 [hp_C]/1 mL; GELSEMIUM SEMPERVIRENS ROOT 34 [hp_C]/1 mL; ZINC 55 [hp_C]/1 mL; POTASSIUM PHOSPHATE, DIBASIC 144 [hp_C]/1 mL; PHOSPHORIC ACID 233 [hp_C]/1 mL; SUS SCROFA TESTICLE 8 [hp_C]/1 mL
INACTIVE INGREDIENTS: WATER; ALCOHOL

MBM 12 Male Unresponsive

ACTIVE INGREDIENT

ACTIVE INGREDIENTS: Chimaphila umbellata 3C, Pituitarinum gland 3C, Uva-ursi 5C, Orchitinum 5C, 8C, Prostate 8C, Sarsaparilla 8C, 55C, Gelsemium sempervirens 34C, Zincum metallicum 55C, Kali phosphoricum 144C, Phosphoricum acidum 233C.

PURPOSE

INDICATIONS: For temporary relief of emotionlessness, denial, numbness, and unresponsiveness.

WARNINGS

WARNINGS: If pregnant or breast-feeding, ask a health professional before use.
Keep out of reach of children. In case of overdose, get medical help or contact a Poison Control Center right away.
Do not use if seal is broken or missing.

DOSAGE AND ADMINISTRATION

DIRECTIONS: Feel the emotion fully, breathe deeply-connected breaths. Put 5 drops under tongue to release emotion. Continue 5 drops 2 times daily as needed. Consult a physician for use in children under 12 years of age.

INACTIVE INGREDIENTS: Demineralized water, 25% Ethanol.

KEEP OUT OF REACH OF CHILDREN: In case of overdose, get medical help or contact a Poison Control Center right away.

INDICATIONS AND USAGE

INDICATIONS: For temporary relief of emotionlessness, denial, numbness, and unresponsiveness.

QUESTIONS

MFD. FOR:

Theresa Cale, N.D.

1237 S. Victoria Ave.

Oxnard, CA 93035

PACKAGE LABEL

Dr. Theresa Dale's

MIND-BODY-MERIDIAN

NDC: 57520-0215-1

Fibonacci Series

12

MBM

Male

Unresponsive

HOMEOPATHIC

1fluid oz. (30 ml)